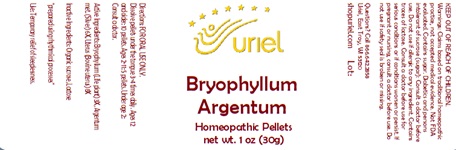 DRUG LABEL: Bryophyllum Argentum
NDC: 48951-2089 | Form: PELLET
Manufacturer: Uriel Pharmacy Inc.
Category: homeopathic | Type: HUMAN OTC DRUG LABEL
Date: 20240513

ACTIVE INGREDIENTS: KALANCHOE DAIGREMONTIANA LEAF 3 [hp_X]/1 1; SILVER 6 [hp_X]/1 1; BOS TAURUS UTERUS 8 [hp_X]/1 1
INACTIVE INGREDIENTS: SUCROSE; LACTOSE

Bryophyllum Argentum

INDICATIONS AND USAGE

Directions: FOR ORAL USE ONLY.

DOSAGE AND ADMINISTRATION

Dissolve pellets under the tongue 3-4 times daily. Ages 12 and older: 10 pellets. Ages 2-11: 5 pellets. Under age 2: Consult
a doctor.

ACTIVE INGREDIENT

Active Ingredients: Bryophyllum (Life plant) 3X, Argentum met. (Silver) 6X, Uterus (Bovine uterus) 8X

Inactive Ingredients: Sucrose, Lactose

"prepared using rhythmical processes"

PURPOSE

Use: Temporary relief of sleeplessness.

KEEP OUT OF REACH OF CHILDREN.

WARNINGS

Warnings: Claims based on traditional homeopathic practice, not accepted medical evidence. Not FDA evaluated. Contains sugar. Diabetics and persons intolerant of sucrose (sugar): Consult a doctor before use. Do not use if allergic to any ingredient. Contains traces of lactose. Consult a doctor before use for serious conditions or if conditions worsen or persist. If pregnant or nursing, consult a doctor before use. Do not use if safety seal is broken or missing.

Questions? Call 866.642.2858
Uriel, East Troy, WI 53120
shopuriel.com Lot: